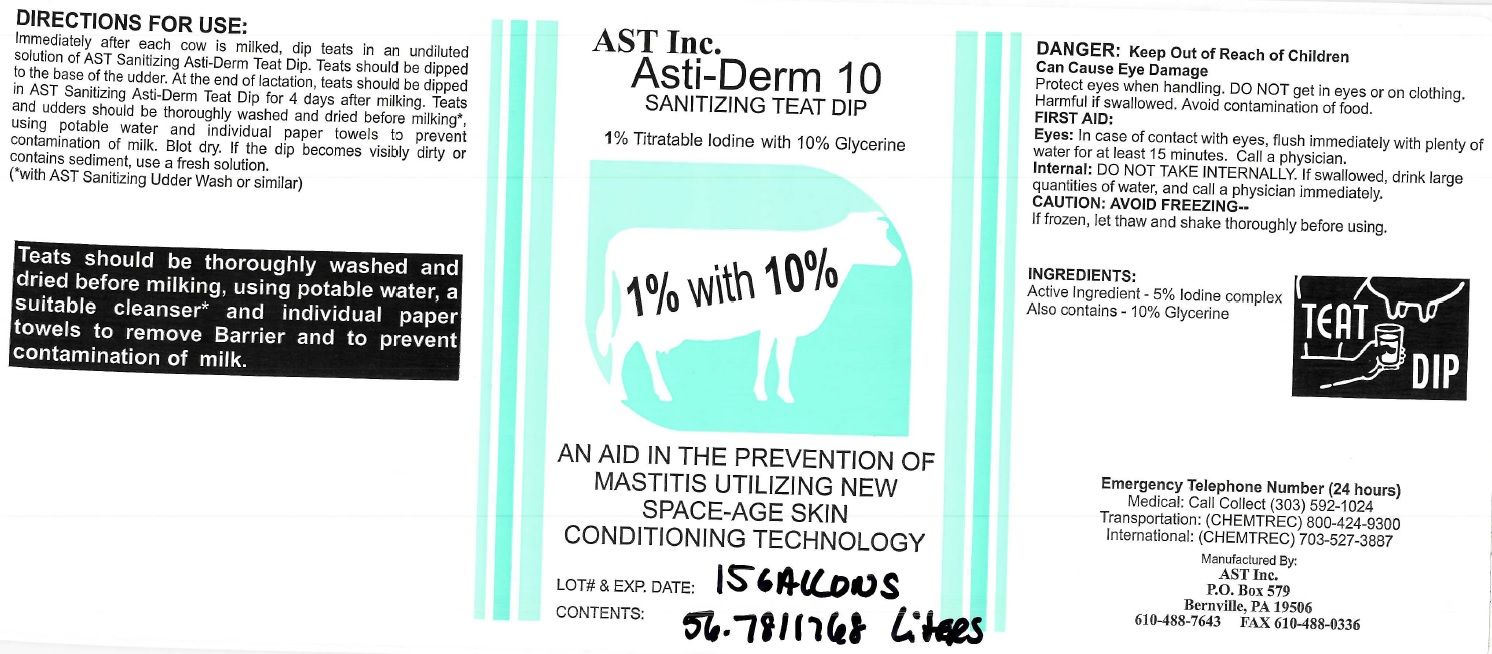 DRUG LABEL: AST Inc. Asti-Derm 10 SANITIZING TEAT DIP
NDC: 52657-0100 | Form: SOLUTION
Manufacturer: Advanced Skin Technologies Inc.
Category: animal | Type: OTC ANIMAL DRUG LABEL
Date: 20221107

ACTIVE INGREDIENTS: IODINE 50 mg/0.001 L
INACTIVE INGREDIENTS: GLYCERIN

AST Inc. Asti-Derm 10 SANITIZING TEAT DIP

DANGER:

Can Cause Eye Damage

Protect eyes when handling. DO NOT get in eyes or on clothing, Harmful if swallowed. Avoid contamination of food.

FIRST AID:

Eyes: In case of contact with eyes, flush immediately with plenty of water for at least 15 minutes. Call a physician.

Internal: DO NOT TAKE INTERNALLY. If swallowed, drink large quantities of water, and call a physician immediately.

CAUTION : AVOID FREEZING--

If frozen, let thaw and shake thoroughly before using.

INGREDIENTS:

Active Ingredient - 5% Iodine complex

Also contains - 10% Glycerine

DIRECTIONS FOR USE:

Immediately after each cow is milked, dip teats in an undiluted solution of AST Sanitizing Asti-Derm Teat Dip. Teats should be dipped to the base of the udder. At the end of lactation, teats should be dipped in AST Sanitizing Asti-Derm Teat Dip for 4 days after milking. Teats and udders should be thoroughly washed and dried before miling*, using potable water and individual paper towels to prevent contamination of milk. Blot dry. If the dip becomes visibly dirty or contains sediment, use a fresh solution.

(*with AST Sanitizing Udder Wash or similar)

Teats should be thoroughly washed and dried before milking, using potable water, a suitable cleanser* and individual paper towels to remove Barrier and to prevent contamination of milk.